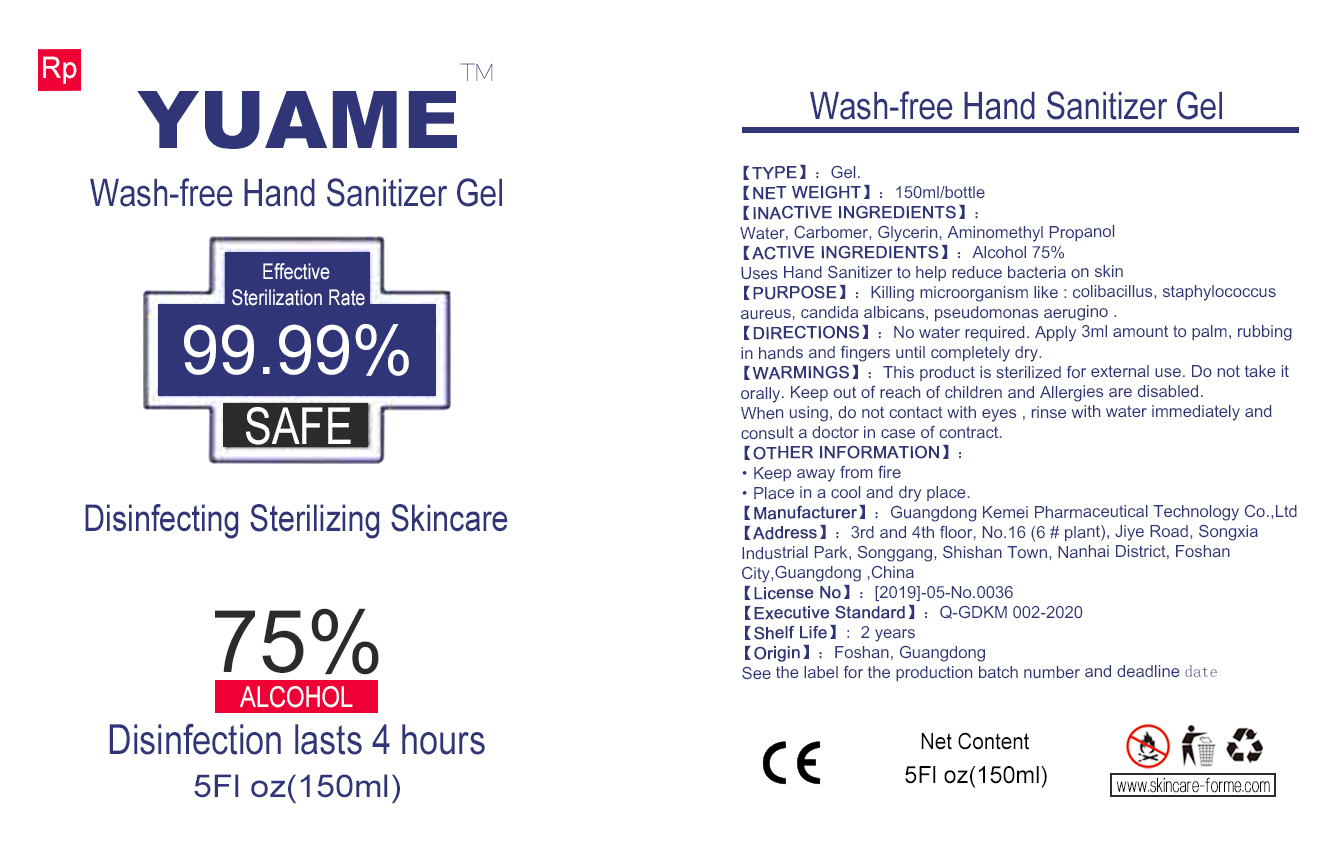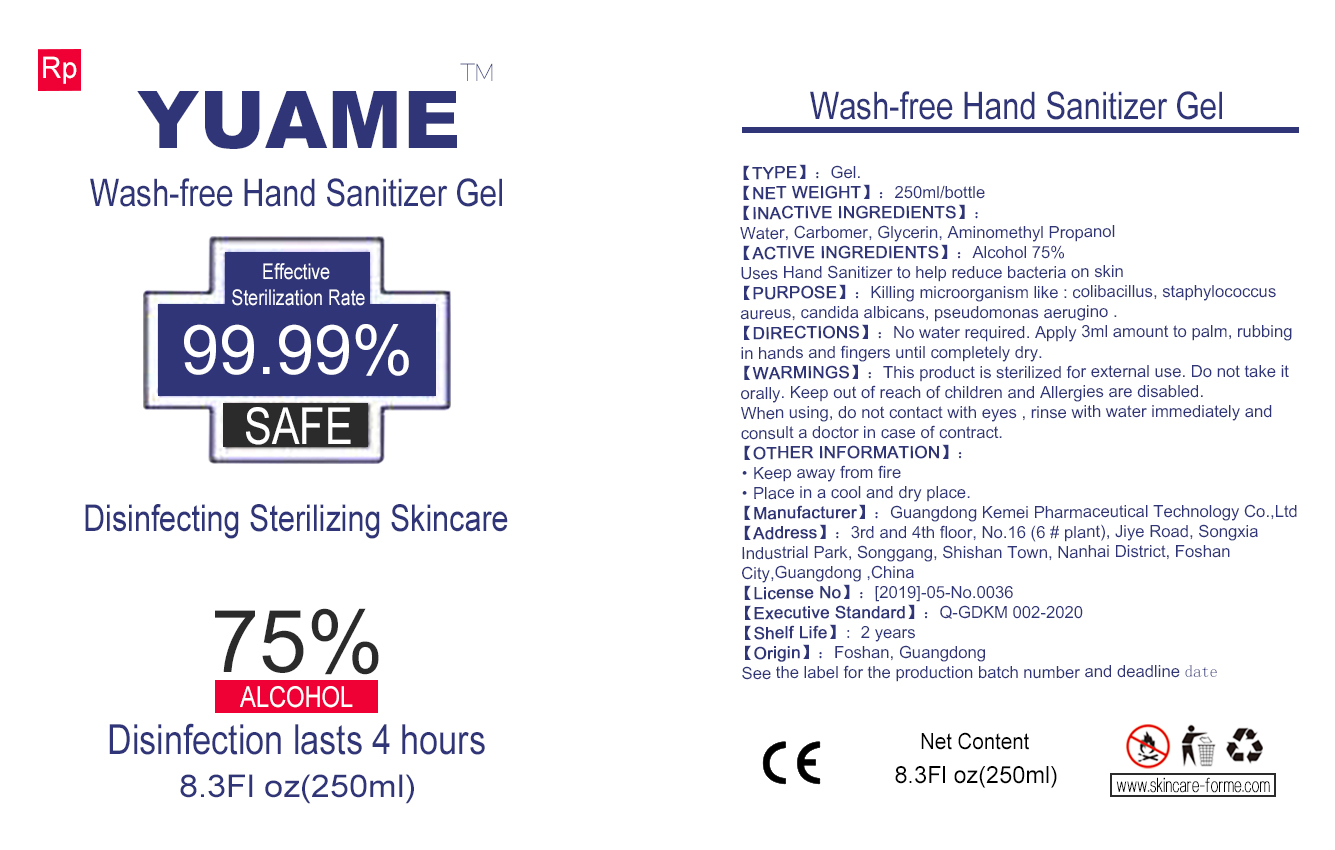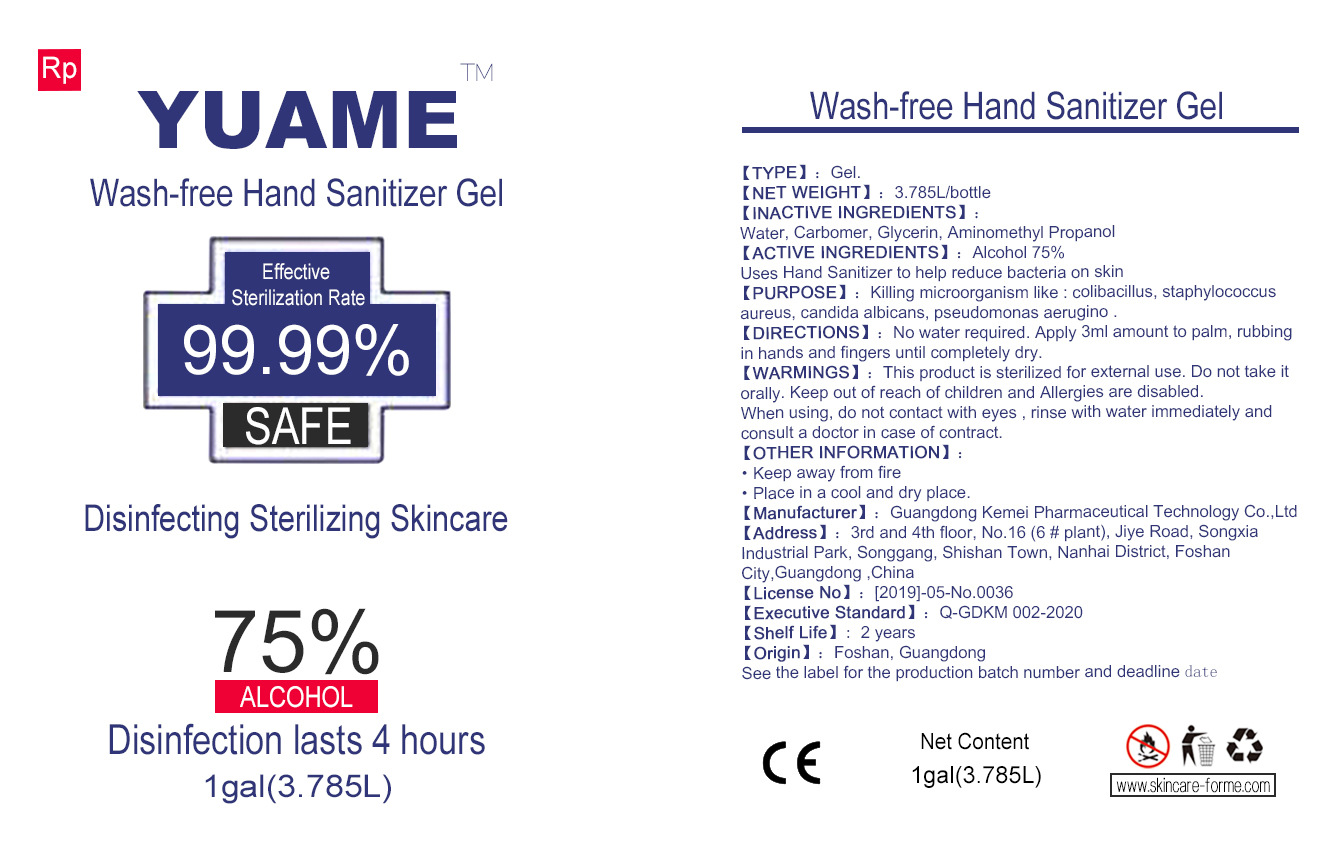 DRUG LABEL: Wash-free Hand Sanitizer Gel
NDC: 75132-011 | Form: GEL
Manufacturer: Guangdong Kemei Pharmaceutical Technology Co., Ltd.
Category: otc | Type: HUMAN OTC DRUG LABEL
Date: 20200522

ACTIVE INGREDIENTS: ALCOHOL 75 mL/100 mL
INACTIVE INGREDIENTS: WATER; CARBOMER HOMOPOLYMER, UNSPECIFIED TYPE; GLYCERIN; AMINOMETHYLPROPANOL

Wash-free Hand Sanitizer Gel

ACTIVE INGREDIENTS

Alcohol 75%

Purpose

Killing microorganism like colibacillus, staphylococcus aureus,candida albicans,

pseudomonas aerugino.

Uses

Uses Hand Sanitizer to help reduce bacteria on skin

Warnings

This product is sterilized for external use.
Do not take it orally.
Keep out of reach of children and Allergies are disabled.
When using, do not contact with eyes, rinse with water immediately and consult a doctor in case of contract.

Do not take it orally.

WHEN USING

When using, do not contact with eyes, rinse with water immediately and consult a doctor in case of contract.

STOP USE

/

Keep out of reach of children and Allergies are disabled.

Directions

No water required.Apply 3ml amount to palm,rubbing in hands and fingers until

completely dry.

Other information

Keep away from fire
Place in a cool and dry place

Inactive ingredients

Water, Carbomer, Glycerin, Aminomethyl Propanol